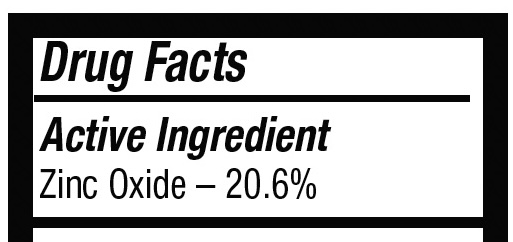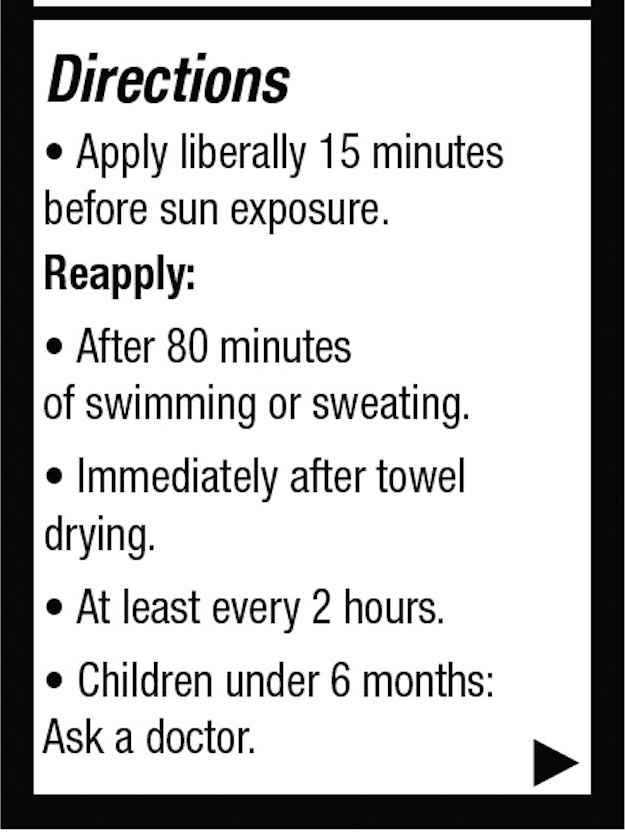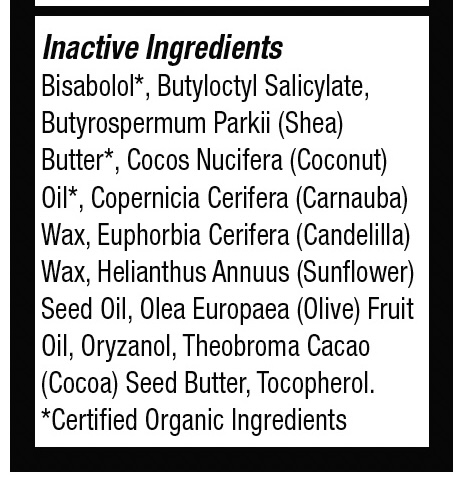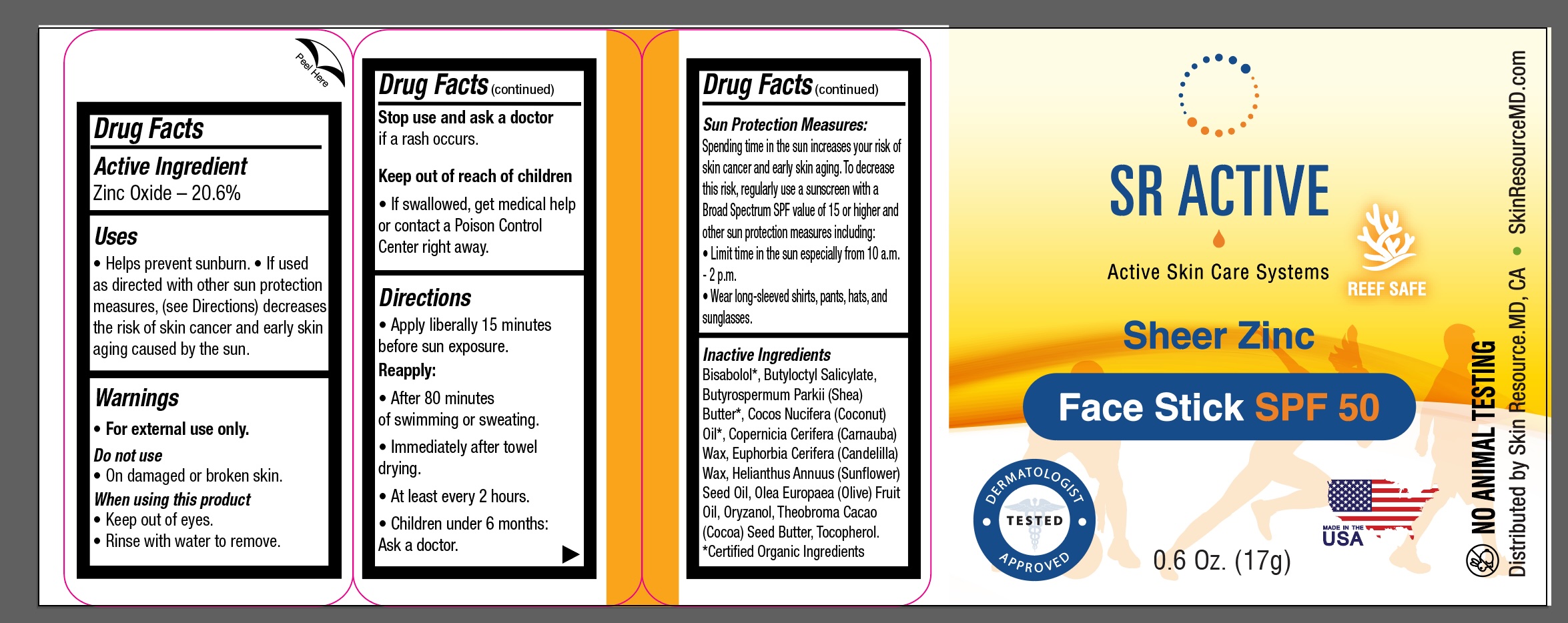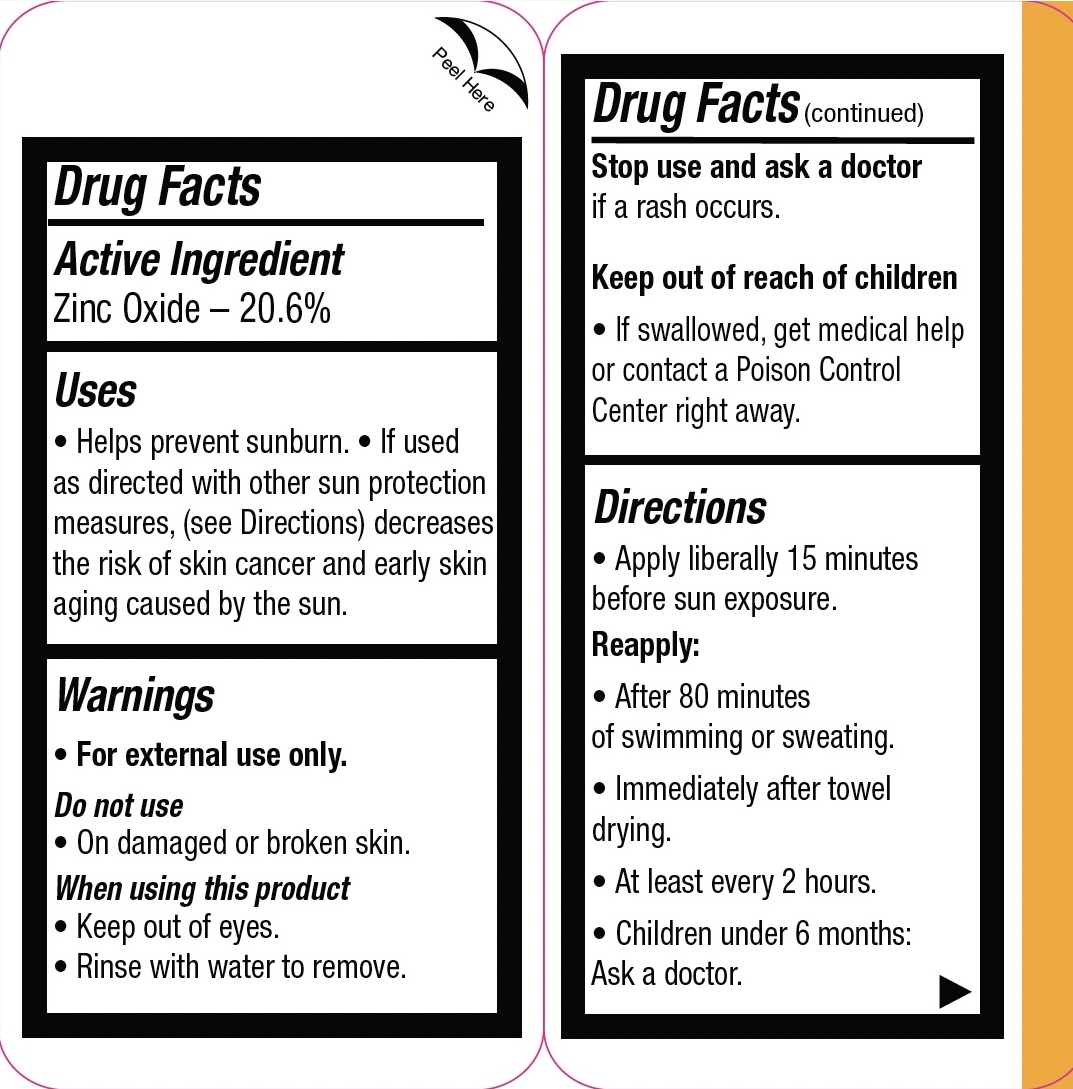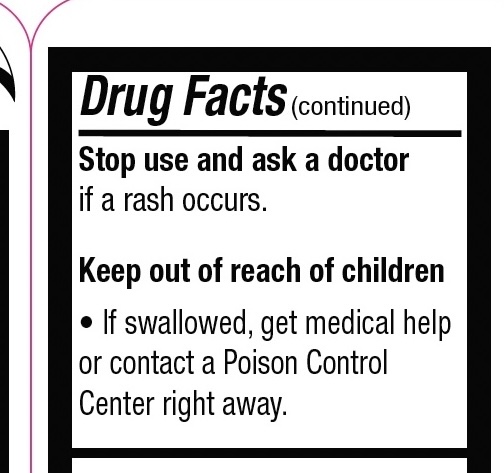 DRUG LABEL: SR Active Sheer Zinc Face Stick SPF 50
NDC: 83694-021 | Form: STICK
Manufacturer: Skinresource.md, L.L.C.
Category: otc | Type: HUMAN OTC DRUG LABEL
Date: 20250625

ACTIVE INGREDIENTS: ZINC OXIDE 3.502 g/17 g
INACTIVE INGREDIENTS: OLEA EUROPAEA (OLIVE) FRUIT OIL; COPERNICIA CERIFERA (CARNAUBA) WAX; EUPHORBIA CERIFERA (CANDELILLA) WAX; ORYZANOL; HELIANTHUS ANNUUS (SUNFLOWER) SEED OIL; THEOBROMA CACAO (COCOA) SEED BUTTER; BUTYLOCTYL SALICYLATE; BISABOLOL; BUTYROSPERMUM PARKII (SHEA) BUTTER; COCOS NUCIFERA (COCONUT) OIL; TOCOPHEROL

ACTIVE INGREDIENTS: Zinc Oxide – 20.6%

Warnings

• For external use only. Do not use
• On damaged or broken skin. When using this product
• Keep out of eyes.
• Rinse with water to remove.

Stop use and ask a doctor
if a rash occurs.

Keep out of reach of children

If swallowed, get medical help or contact a Poison Control Center right away.

Inactive Ingredients:
Bisabolol*
Butyloctyl Salicylate
Butyrospermum Parkii (Shea) Butter*
Cocos Nucifera (Coconut) Oil*
Copernicia Cerifera (Carnauba) Wax
Euphorbia Cerifera (Candelilla) Wax
Helianthus Annuus (Sunflower) Seed Oil
Olea Europaea (Olive) Fruit Oil
Oryzanol
Theobroma Cacao (Cocoa) Seed Butter
Tocopherol
*Certified Organic Ingredients

PURPOSE

Zinc Oxide - 20.6% Sunscreen

Keep Out of Reach of Children

If swallowed, get medical help or contact a Poison Control Center right away.

INDICATIONS AND USAGE

Helps prevent sunburn. • If used as directed with other sun protection measures, (see Directions) decreases the risk of skin cancer and early skin aging caused by the sun.

Sun Protection Measures:

Spending time in the sun increases your risk of skin cancer and early skin aging. To decrease this risk, regularly use a sunscreen with a Broad Spectrum SPF value of 15 or higher and other sun protection measures including:

Limit time in the sun especially from 10 a.m.

2 p.m.

Wearlong-sleved shirts, pants, hats, and sunglasses.

• For external use only.

Do not use

• On damaged or broken skin.

When using this product

Keep out of eyes.
Rinse with water to remove.

DOSAGE AND ADMINISTRATION

Apply liberally 15 minutes before sun exposure.
Reapply:
• After 80 minutes of swimming or sweating.
• Immediately after towel drying.
• At least every 2 hours.
• Children under 6 months: Ask a doctor.

SR Active Face Stick

Package Label